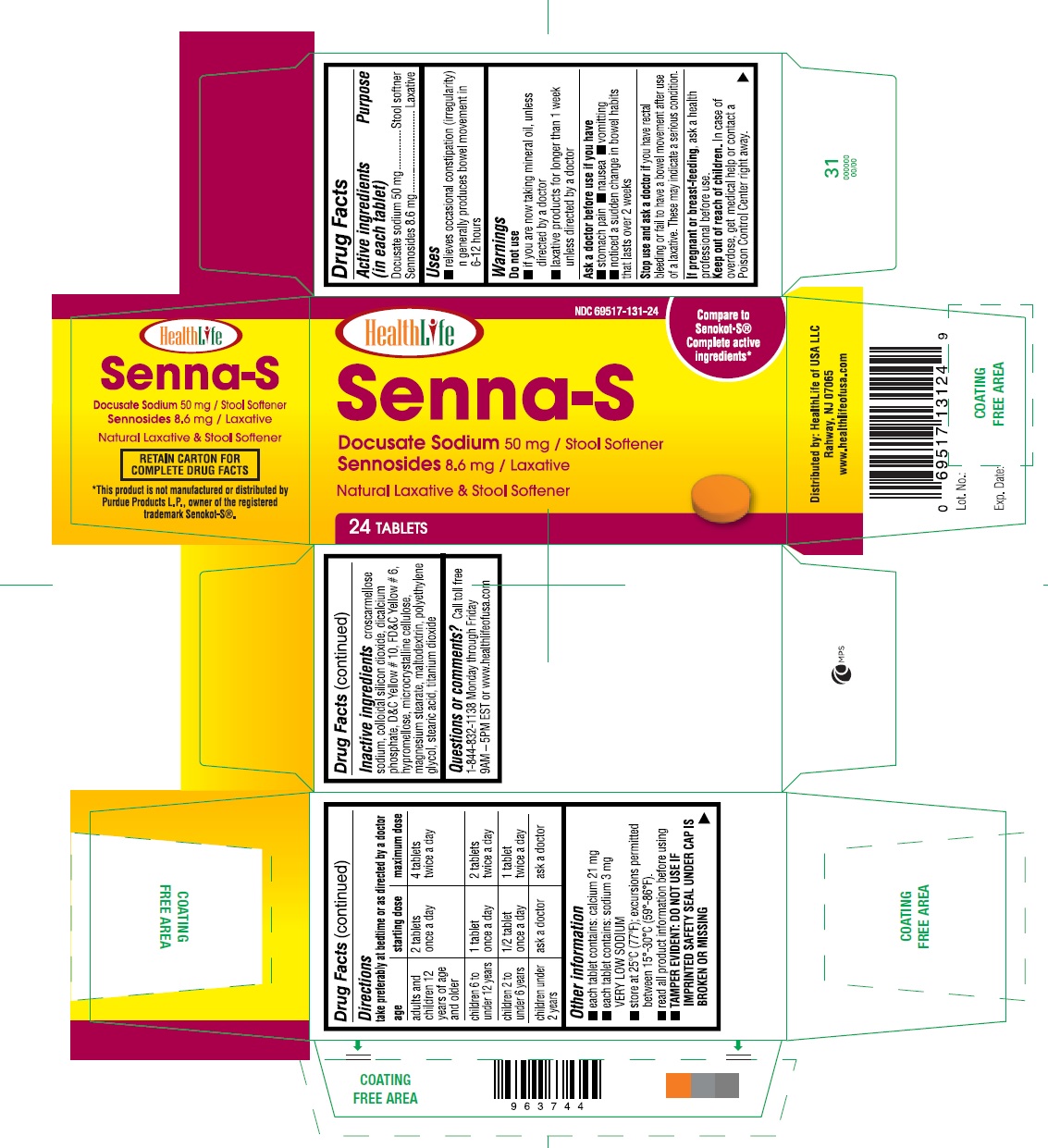 DRUG LABEL: SENNA-S
NDC: 69517-131 | Form: TABLET, COATED
Manufacturer: HealthLife of USA LLC
Category: otc | Type: HUMAN OTC DRUG LABEL
Date: 20231021

ACTIVE INGREDIENTS: SENNOSIDES 8.6 mg/1 1; DOCUSATE SODIUM 50 mg/1 1
INACTIVE INGREDIENTS: CROSCARMELLOSE SODIUM; SILICON DIOXIDE; CALCIUM PHOSPHATE, DIBASIC, DIHYDRATE; D&C YELLOW NO. 10; FD&C YELLOW NO. 6; HYPROMELLOSES; CELLULOSE, MICROCRYSTALLINE; MAGNESIUM STEARATE; MALTODEXTRIN; POLYETHYLENE GLYCOL 1000; STEARIC ACID; TITANIUM DIOXIDE

Senna-S - Senna and Docusate Sodium Tablets, 8.6 mg & 50 mg

Drug Facts

ACTIVE INGREDIENT

Active ingredients Purpose (in each tablet) Purpose

Docusate sodium 50 mg.......................................Stool softner

Sennosides 8.6 mg................................................Laxative

Uses

- relieves occasional constipation (irregularity)
- generally produces bowel movement in 6-12 hours

Warnings

Do not use

- if you are now taking mineral oil, unless directed by a doctor
- laxative products for longer than 1 week unless directed by a doctor

Ask a doctor before use if you have

- stomach pain
- nausea
- vomiting
- noticed a sudden change in bowel habits that lasts over 2 weeks

Stop use and ask a doctor if

you have rectal bleeding or fail to have a bowel movement after use of a laxative. These may indicate a serious condition.

PREGNANCY OR BREAST FEEDING

If pregnant or breast-feeding, ask a health professional before use.

Keep out of reach of children.

In case of overdose, get medical help or contact a Poison Control Center right away.

Directions

take preferably at bedtime or as directed by a doctor

- adults and children 12 years of age or older- starting dosage:2 tablets once a day, maximum dosage:4 tablets twice a day
- children 6 to under 12 years- starting dosage:1 tablet once a day, maximum dosage:2 tablets twice a day
- children 2 to under 6 years- starting dosage:1/2 tablet once a day, maximum dosage:1 tablet twice a day
- children under 2 years- starting dosage:ask a doctor, maximum dosage:ask a doctor

Other information

- each tablet contains: calcium 21 mg
- each tablet contains: sodium 3 mg VERY LOW SODIUM
- store at 25ºC (77ºF); excursions permitted between 15°-30°C (59°-86°F)
- read all product information before using
- TAMPER EVIDENT: DO NOT USE IF IMPRINTED SAFETY SEAL UNDER CAP IS BROKEN OR MISSING

Inactive ingredients

croscarmellose sodium, colloidal silicon dioxide, dicalcium phosphate, D&C Yellow # 10, FD&C Yellow # 6, hypromellose, microcrystalline cellulose, magnesium stearate, maltodextrin, polyethylene glycol, stearic acid, titanium dioxide

Questions or comments?

Call toll free 1-844-832-1138 Monday through Friday 9AM – 5PM EST or www.healthlifeofusa.com

PRINCIPAL DISPLAY PANEL

Compare to the Active Ingredients in Senokot-S®

*This product is not manufactured or distributed by Purdue Products L.P., owner of the registered trademark Senokot-S®.

Senna and Docusate Sodium Tablets, 8.6 mg and 50 mg